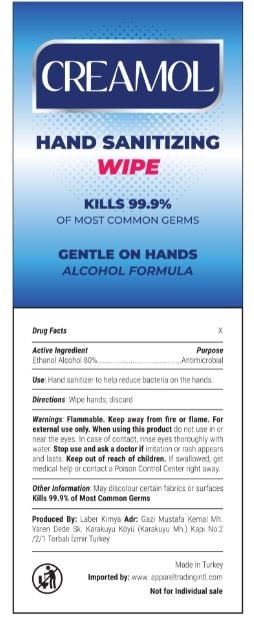 DRUG LABEL: CREAMOL HAND SANITIZING WIPE
NDC: 77892-020 | Form: SWAB
Manufacturer: Laber Kimya AR-GE Sanayi Ticaret Levent KAHRIMAN
Category: otc | Type: HUMAN OTC DRUG LABEL
Date: 20201118

ACTIVE INGREDIENTS: ALCOHOL 80 g/100 g
INACTIVE INGREDIENTS: GLYCERIN; HYPERICUM PERFORATUM WHOLE; MELALEUCA ALTERNIFOLIA LEAF; WATER

CREAMOL HAND SANITIZING WIPE

Active Ingredient(s)

Alcohol 80% w/w. Purpose: Antiseptic

Purpose

Antiseptic, Hand Sanitizer

Use

Hand Sanitizer to help reduce bacteria that potentially can cause disease. For use when soap and water are not available.

Warnings

For external use only. Flammable. Keep away from heat or flame

Do not use

- in children less than 2 months of age
- on open skin wounds

When using this product keep out of eyes, ears, and mouth. In case of contact with eyes, rinse eyes thoroughly with water.

Stop use and ask a doctor if irritation or rash occurs. These may be signs of a serious condition.

Keep out of reach of children. If swallowed, get medical help or contact a Poison Control Center right away.

Directions

Wipe hands; discard

Other information

- Store between 15-30C (59-86F)
- Avoid freezing and excessive heat above 40C (104F)

Inactive ingredients

Aqua, Glycerin, Melaleuca Alternifolia Leaf Extract, Hypericum Perforatum Extract